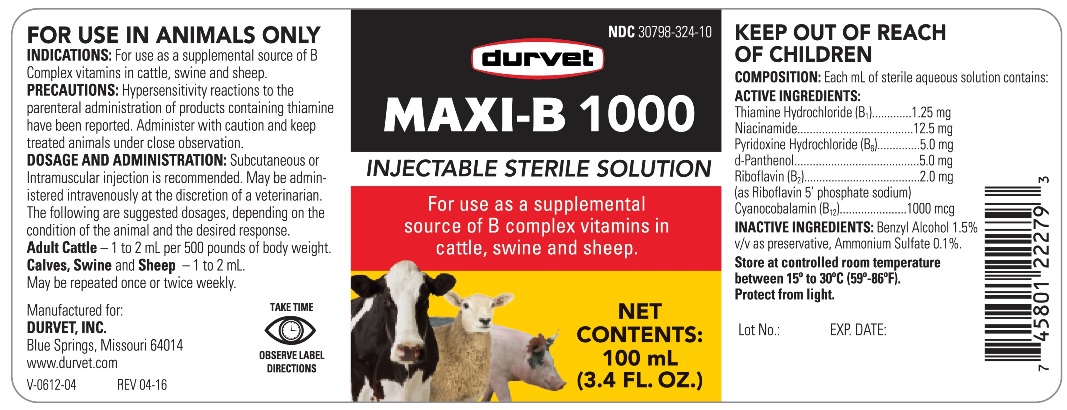 DRUG LABEL: MAXI-B
NDC: 30798-324 | Form: INJECTION
Manufacturer: Durvet, Inc.
Category: animal | Type: OTC ANIMAL DRUG LABEL
Date: 20180307

ACTIVE INGREDIENTS: CYANOCOBALAMIN 1000 ug/1 mL; NIACINAMIDE 12.5 mg/1 mL; DEXPANTHENOL 5.0 mg/1 mL; PYRIDOXINE HYDROCHLORIDE 5.0 mg/1 mL; RIBOFLAVIN 5'-PHOSPHATE SODIUM 2.0 mg/1 mL; THIAMINE HYDROCHLORIDE 1.25 mg/1 mL

MAXI-B 1000

INDICATIONS AND USAGE

INJECTABLE STERILE SOLUTION

FOR USE IN ANIMALS ONLY

KEEP OUT OF REACH OF CHILDREN

INDICATIONS

For use as a supplemental source of Bcomplex vitamins in cattle, swine and sheep.

PRECAUTIONS

Hypersensitivity reactions to the parenteral administration of products containing thiamine have been reported. Administer with caution and keep treated animals under close observation.

DOSAGE AND ADMINISTRATION

Subcutaneous or Intramuscular injection is recommended. May be administered intravenously at the discretion of a veterinarian. The following are suggested dosages depending on the condition of the animal and the desired response.

Adult Cattle-1 to 2 mL per 500 pounds of body weight

Calves, Swine and Sheep-1 to 2 mL. May be repeated once or twice weekly.

COMPOSITION

Each mL of sterile aqueous solution contains:

Thiamine Hydrochloride (B1) ............ 1.25 mg
Niacinamide ................................... 12.5 mg
Pyridoxine Hydrochloride (B6) ............ 5.0 mg
d-Panthenol ..................................... 5.0 mg
Riboflavin (B2) ................................. 2.0 mg
(as Riboflavin 5' phosphate sodium)
Cyanocobalamin (B12) ................... 1000 mcg

INACTIVE INGREDIENTS

Benzyl Alcohol 1.5% v/v as preservative, Ammonium Sulfate 0.1%.

STORAGE AND HANDLING

Store at controlled room temperature between 15° and 30°C (59°-86°)

Protect from sunlight.

TAKE TIME OBSERVE LABEL DIRECTIONS